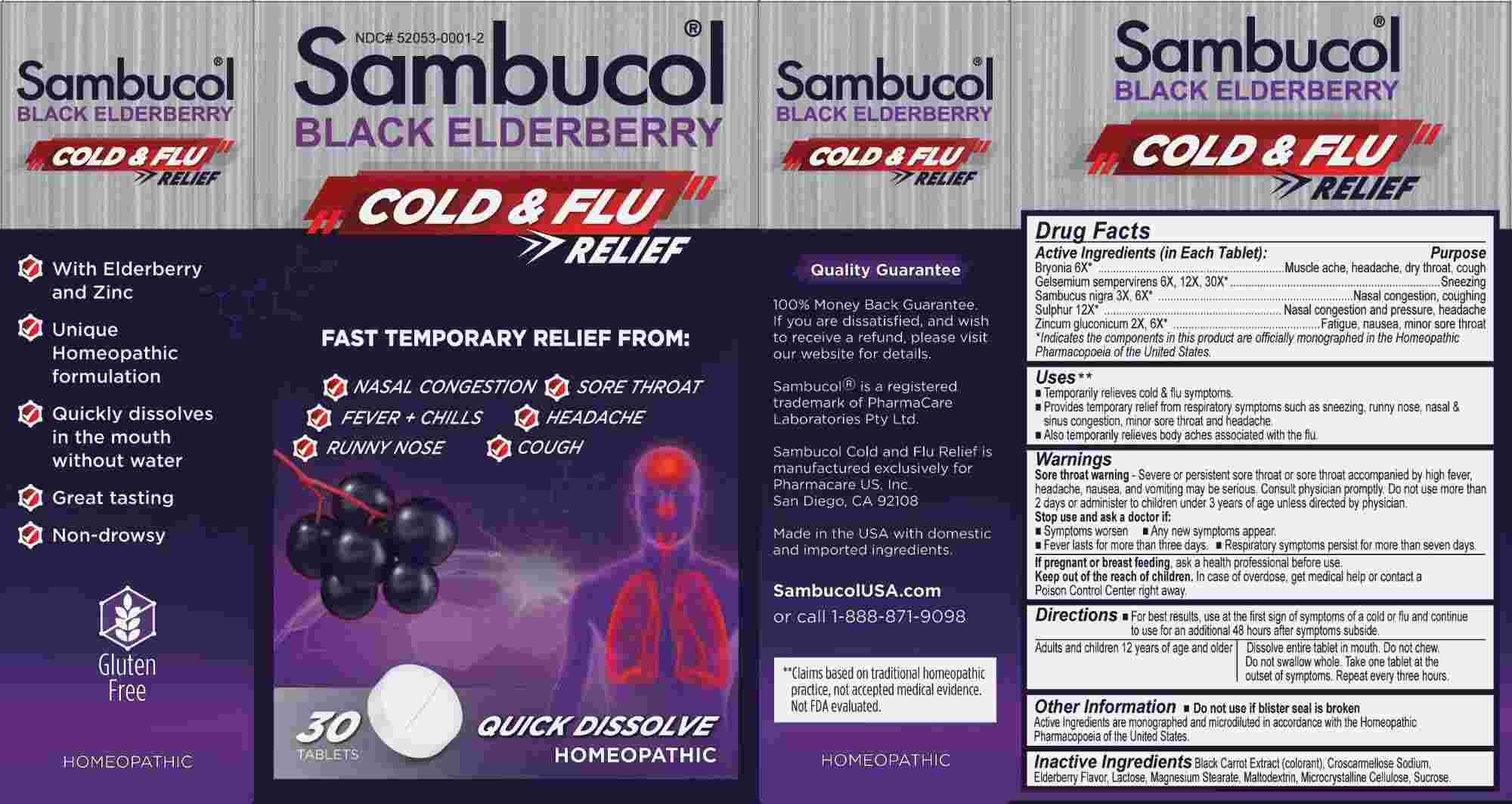 DRUG LABEL: Sambucol Cold and Flu Relief
NDC: 52053-0001 | Form: TABLET, ORALLY DISINTEGRATING
Manufacturer: PharmaCare US, Inc.
Category: homeopathic | Type: HUMAN OTC DRUG LABEL
Date: 20241104

ACTIVE INGREDIENTS: BRYONIA ALBA ROOT 6 [hp_X]/1 mg; GELSEMIUM SEMPERVIRENS ROOT 6 [hp_X]/1 mg; SAMBUCUS NIGRA FLOWERING TOP 3 [hp_X]/1 mg; SULFUR 12 [hp_X]/1 mg; ZINC GLUCONATE 2 [hp_X]/1 mg
INACTIVE INGREDIENTS: BLACK CARROT ANTHOCYANINS; CROSCARMELLOSE SODIUM; LACTOSE; MAGNESIUM STEARATE; MALTODEXTRIN; CELLULOSE, MICROCRYSTALLINE; SUCROSE; EUROPEAN ELDERBERRY JUICE

DRUG FACTS:

ACTIVE INGREDIENTS:

(in Each Tablet): Bryonia 6X,* Gelsemium Sempervirens 6X, 12X, 30X,* Sambucus Nigra 3X, 6X,* Sulphur 12X,* Zincum Gluconicum 2X, 6X.*
*Indicates the components in this product are officially monographed in the Homeopathic Pharmacopoeia of the United States.

PURPOSE:

Bryonia – Muscle ache, headache, dry throat, cough, Gelsemium Sempervirens - Sneezing, Sambucus Nigra – Nasal congestion, coughing, Sulphur – Nasal congestion and pressure, headache, Zincum Gluconicum – Fatigue, nausea, minor sore throat.

USES:

• Temporarily relieves cold & flu symptoms.**

• Provides temporary relief from respiratory symptoms such as sneezing, runny nose, nasal & sinus congestion, minor sore throat and

headache.**

• Also temporarily relieves body aches associated with the flu.**

**Claims based on traditional homeopathic practice, not accepted medical evidence. Not FDA evaluated.

WARNINGS:

Sore throat warning - Severe or persistent sore throat or sore throat accompanied by high fever, headache, nausea, and vomiting may be serious. Consult physician promptly. Do not use more than 2 days or administer to children under 3 years of age unless directed by a physician. Stop use and ask a doctor if:

• Symptoms worsen • Any new symptoms appear.

• Fever lasts for more than three days.

• Respiratory symptoms persist for more than seven days.

If pregnant or breast feeding, ask a health professional before use.

Keep out of reach of children. In case of overdose, get medical help or contact a Poison Control Center right away.

Do not use if blister seal is broken.

Active Ingredients are monographed and microdiluted in accordance with the Homeopathic Pharmacopoeia of the United States.

KEEP OUT OF REACH OF CHILDREN:

In case of overdose, get medical help or contact a Poison Control Center right away.

DIRECTIONS:

• For best results, use at the first sign of symptoms of a cold or flu and continue to use for an additional 48 hours after symptoms subside.

Adults and children 12 years of age and older. Dissolve entire tablet in mouth. Do not chew. Do not swallow whole. Take one tablet at the outset of symptoms. Repeat every three hours.

INACTIVE INGREDIENTS:

Black Carrot Extract (Colorant), Croscarmellose Sodium, Elderberry Flavor, Lactose, Magnesium Stearate, Maltodextrin, Microcrystalline Cellulose, Sucrose.

QUESTIONS:

Manufactured exclusively for

Pharmacare US, Inc.

San Diego, CA 92108

SambucolUSA.com or

call 1-888-871-9098

PACKAGE LABEL DISPLAY:

NDC# 52053-0001-2
Sambucol®
BLACK ELDERBERRY
COLD & FLU RELIEF

FAST TEMPORARY RELIEF FROM:

√ NASAL CONGESTION √ SORE THROAT

√ FEVER + CHILLS √ HEADACHE

√ RUNNY NOSE √ COUGH

30 TABLETS

HOMEOPATHIC